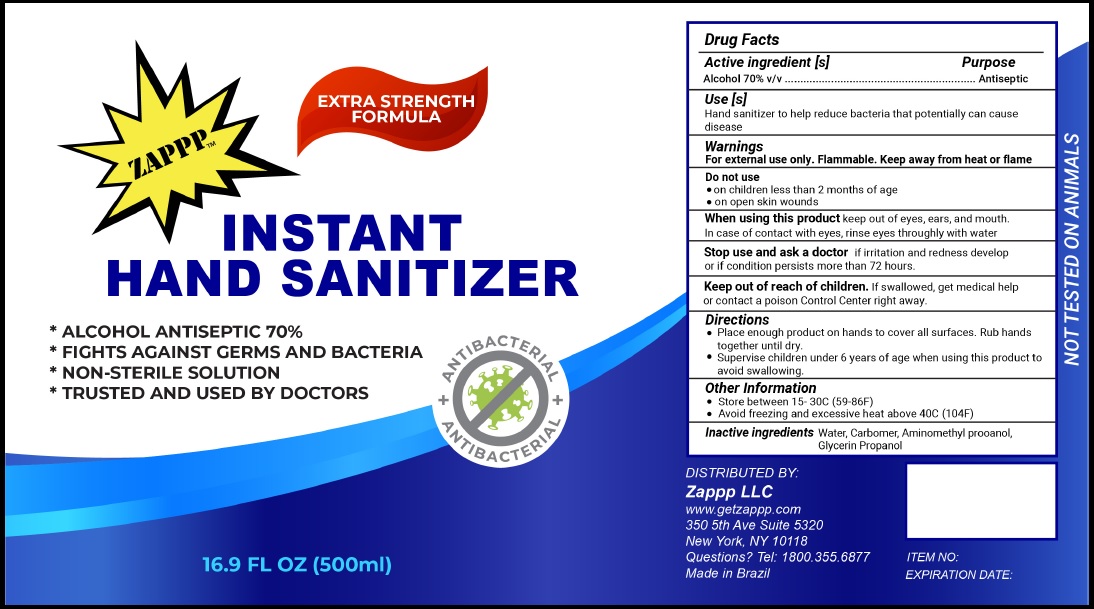 DRUG LABEL: ZAPPP instant hand sanitizer
NDC: 78467-001 | Form: GEL
Manufacturer: LUSINE INDUSTRIA E COMERCIO DE COSMETICOS EIRELI
Category: otc | Type: HUMAN OTC DRUG LABEL
Date: 20200812

ACTIVE INGREDIENTS: ALCOHOL 70 mL/100 mL
INACTIVE INGREDIENTS: CARBOMER HOMOPOLYMER TYPE C (ALLYL PENTAERYTHRITOL CROSSLINKED); WATER; GLYCERIN; AMINOMETHYLPROPANOL; DENATONIUM BENZOATE

Active Ingredient

Alcohol 70% v/v.

Purpose

Antiseptic

Use

Hand sanitizer to help reduce bacteria that potentially can cause disease.

Warnings

For external use only. Flammable. Keep away from heat or flame

Do not use

- in children less than 2 months of age.
- on open skin wounds.

When using this product keep out of eyes, ears, and mouth. In case of contact with eyes, rinse eyes thoroughly with water.

Stop use and ask doctor if irritation and redness develop or if condition persists more than 72 hours.

Keep out of reach of children. If swallowed, get medical help or contact a Poison Control Center right away.

Directions

- Place enough product on hands to cover all surfaces. Rub hands together until dry.
- Supervise children under 6 years of age when using this product to avoid swallowing.

Other information

- Store between 15-30C (59-86F)
- Avoid freezing and excessive heat above 40C (104F)

Inactive ingredients

Carbomer, Water, Glycerin, Aminomethylpropanol, Denatonium benzoate